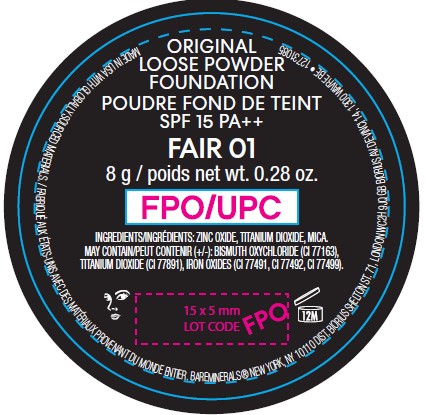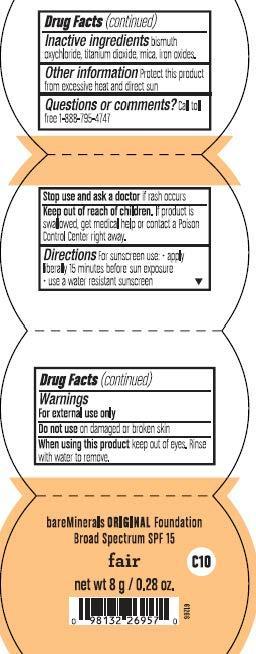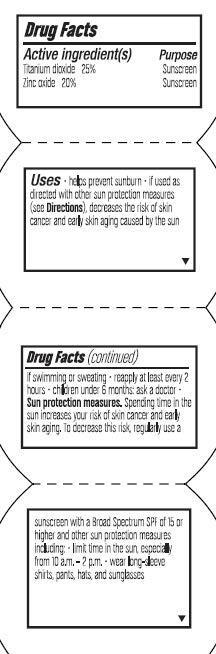 DRUG LABEL: Fair Foundation SPF 15
NDC: 98132-871 | Form: POWDER
Manufacturer: Orveon Global US, LLC
Category: otc | Type: HUMAN OTC DRUG LABEL
Date: 20231004

ACTIVE INGREDIENTS: ZINC OXIDE 19 g/100 g; TITANIUM DIOXIDE 25 g/100 g
INACTIVE INGREDIENTS: MICA; BISMUTH OXYCHLORIDE; BROWN IRON OXIDE; FERRIC OXIDE YELLOW

BareMineral Original SPF 15 Foundation Fair

Drug Facts

Active Ingredients

Titanium Dioxide 25%

Zinc Oxide 19%

Purpose

Sunscreen

Uses

- Helps prevent sunburn
- If used as directed with other sun protection measures (see Directions), decreases the risk of skin cancer and early skin aging caused by the sun

Warnings

- Skin cancer/skin aging alert: spending time in the sun increases your risk of cancer and early aging
- This product has been shown only to help prevent sunburn, not skin cancer or early aging
- For External use only
- Do not use on damage or broken skin
- When using this product keep out of eyes. Rinse with water to remove
- Stop use and ask doctor if rash occurs

Inactive ingredients

Bismuth Oxychloride, Iron Oxides, Mica, Titanium Dioxide, Zinc Oxide

Questions or Comments?

Call toll free 1-888-795-4747

Directions

Apply liberally 15 minutes before sun exposure
Use a water-resistant sunscreen if swimming or sweating
Reapply at least every 2 hours
Sun protection measures. Spending time in the sun increases your risk of skin cancer or early skin aging. To decrease this risk, regularly use a a sunscreen with a broad spectrum SPF of 15 or higher and other sun protection measures including:
Limit time in the sun, especially from 10 a.m. - 2 p.m.
Wear long sleeve shirts, pants, hats, and sunglasses
Children under 6 month: ask a doctor

Keep out of reach of children.

If product is swallowed get medical help or contact a poison control center right away.